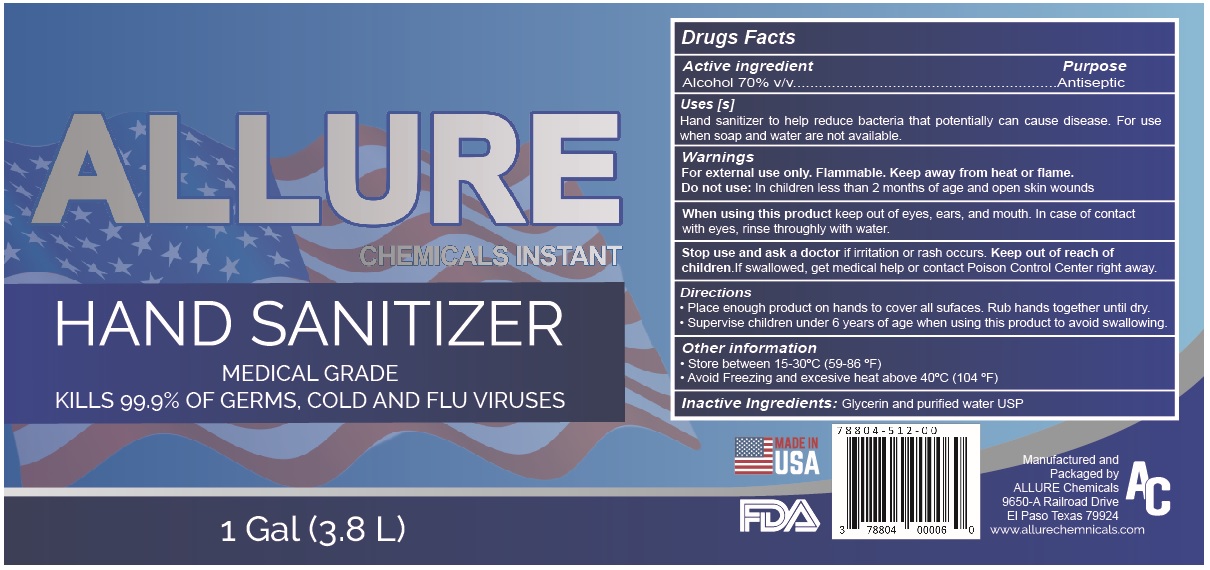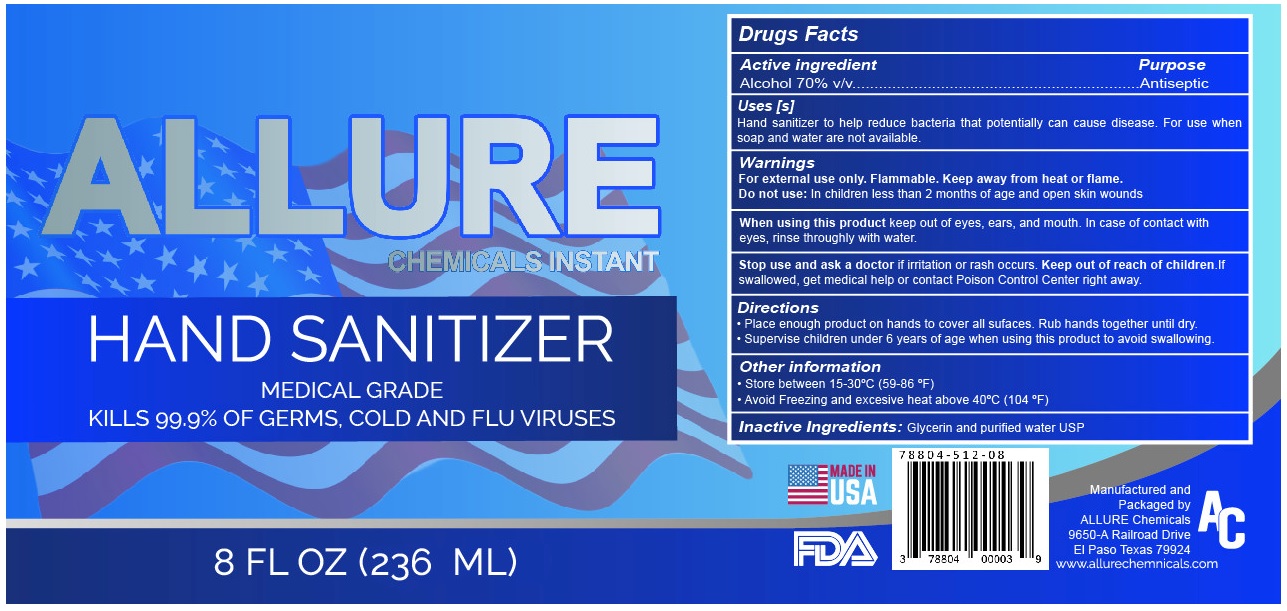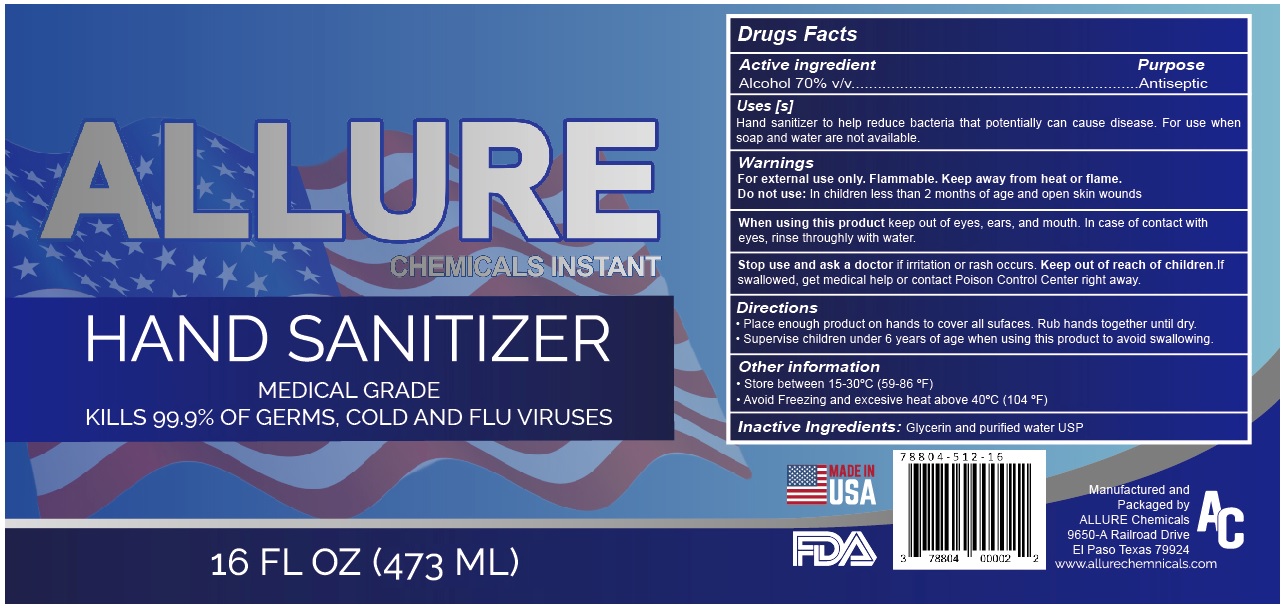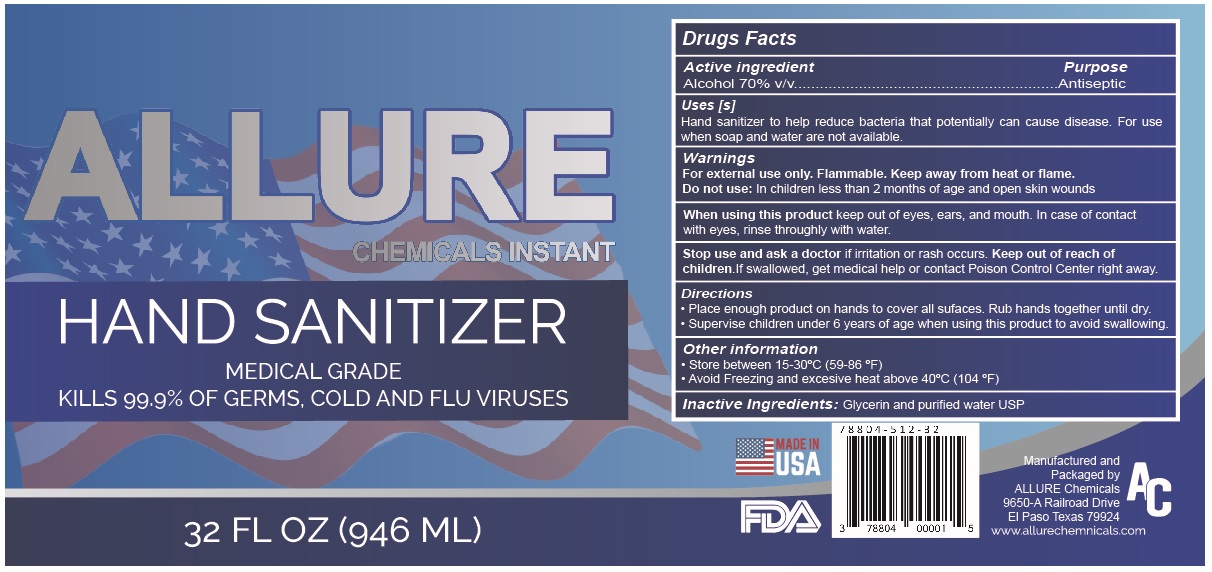 DRUG LABEL: ALLURE CHEMICALS INSTANT HAND SANITIZER
NDC: 78804-512 | Form: SOLUTION
Manufacturer: Allure Chemicals LP
Category: otc | Type: HUMAN OTC DRUG LABEL
Date: 20200826

ACTIVE INGREDIENTS: ALCOHOL 700 mL/1 L
INACTIVE INGREDIENTS: GLYCERIN; WATER

ALLURE CHEMICALS INSTANT HAND SANITIZER

Active Ingredient[s]

Alcohol 70% v/v

Purpose

Antiseptic

Use[s]

Hand sanitizer to help reduce bacteria that potentially can cause disease. For use when soap and water are not available.

Warnings

For external use only. Flammable. Keep away from heat or flame.

Do not use: In children less than 2 months of age and open skin wounds

When using this product keep out of the eyes, ears, and mouth. In case of contact with eyes, rinse eyes thoroughly with water.

Stop use and ask a doctor if irritation or rash occurs.

Keep out of reach of children. If swallowed, get medical help or contact Poison Control Center right away.

Directions

• Place enough product on hands to cover all surfaces. Rub hands together until dry.

• Supervise children under 6 years of age when using this product to avoid swallowing.

Other information

• Store between 15-30°C (59-86 °F)

• Avoid freezing and excessive heat above 40°C (104 °F)

Inactive ingredients

Glycerin, and purified water USP

MEDICAL GRADE

KILLS 99.9% OF GERMS, COLD AND FLU VIRUSES

MADE IN USA

Manufactured and Packaged by

ALLURE Chemicals

9650-A Railroad Drive

EI Paso Texas 79924

www.allurechemicals.com